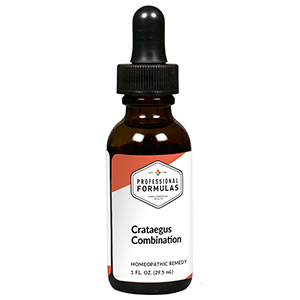 DRUG LABEL: Crataegus Combination
NDC: 63083-9220 | Form: LIQUID
Manufacturer: Professional Complementary Health Formulas
Category: homeopathic | Type: HUMAN OTC DRUG LABEL
Date: 20190815

ACTIVE INGREDIENTS: HAWTHORN LEAF WITH FLOWER 1 [hp_X]/29.5 mL; SPIGELIA ANTHELMIA WHOLE 2 [hp_X]/29.5 mL; POTASSIUM CARBONATE 3 [hp_X]/29.5 mL; ARNICA MONTANA WHOLE 4 [hp_X]/29.5 mL; SELENICEREUS GRANDIFLORUS STEM 4 [hp_X]/29.5 mL; GELSEMIUM SEMPERVIRENS ROOT 4 [hp_X]/29.5 mL; CASTOR FIBER SCENT GLAND SECRETION 6 [hp_X]/29.5 mL; NITROGLYCERIN 6 [hp_X]/29.5 mL; RANUNCULUS BULBOSUS WHOLE 6 [hp_X]/29.5 mL; SULFUR 12 [hp_X]/29.5 mL
INACTIVE INGREDIENTS: ALCOHOL; WATER

R220

ACTIVE INGREDIENTS

Crataegus 1X
Spigelia anthelmia 2X
Kali carbonicum 3X
Arnica montana 4X
Cactus grandiflorus 4X
Gelsemium sempervirens 4X
Castoreum 6X
Glonoinum 6X
Ranunculus bulbosus 6X
Sulphur 12X

QUESTIONS

Professional Formulas

PO Box 2034 Lake Oswego, OR 97035

INDICATIONS

For the temporary relief of occasional insomnia, restlessness, or anxiousness.*

PURPOSE

*Claims based on traditional homeopathic practice, not accepted medical evidence. Not FDA evaluated.

WARNINGS

In case of overdose, get medical help or contact a poison control center right away.

Keep out of the reach of children.

PREGNANCY OR BREAST FEEDING

If pregnant or breastfeeding, ask a healthcare professional before use.

DIRECTIONS

Place drops under tongue 30 minutes before/after meals. Adults and children 12 years and over: Take 10 drops up to 3 times per day. Consult a physician for use in children under 12 years of age.

OTHER INFORMATION

Tamper resistant. If seal is broken, do not use. After opening, close container tightly and store at room temperature away from heat.

INACTIVE INGREDIENTS

40% ethanol, purified water.

LABEL

Est 1985

Professional Formulas

Complementary Health

Crataegus Combination

Homeopathic Remedy

1 FL. OZ. (29.5 mL)